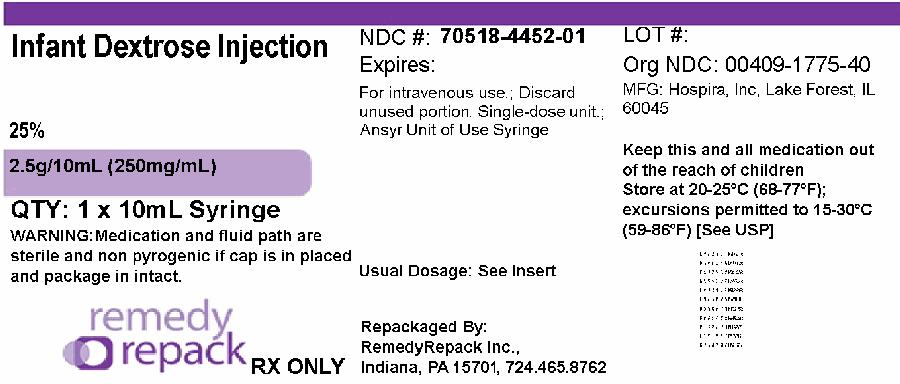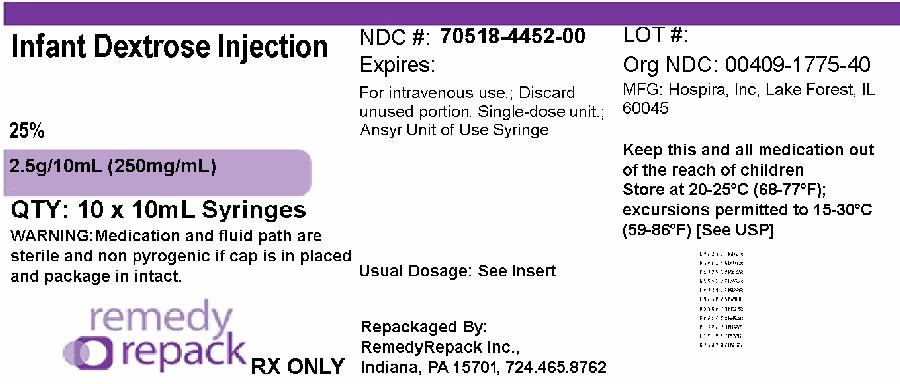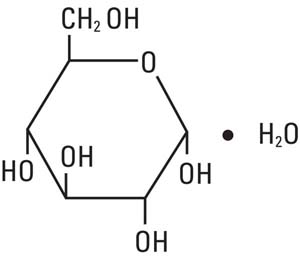 DRUG LABEL: Dextrose
NDC: 70518-4452 | Form: INJECTION, SOLUTION
Manufacturer: REMEDYREPACK INC.
Category: prescription | Type: HUMAN PRESCRIPTION DRUG LABEL
Date: 20250825

ACTIVE INGREDIENTS: DEXTROSE MONOHYDRATE 250 mg/1 mL
INACTIVE INGREDIENTS: WATER; HYDROCHLORIC ACID; SODIUM HYDROXIDE

HIGHLIGHTS OF PRESCRIBING INFORMATION

These highlights do not include all the information needed to use DEXTROSE INJECTION (25%) safely and effectively. See full prescribing information for DEXTROSE INJECTION (25%).
Initial U.S. Approval: 1940

RECENT MAJOR CHANGES

Dosage and Administration (2.1, 2.2) | 07/2025
Contraindications (4) | 07/2025
Warnings and Precautions (5.1, 5.2, 5.3, 5.4, 5.5, 5.6) | 07/2025

1 INDICATIONS AND USAGE

Dextrose Injection (25%) is indicated for the treatment of acute symptomatic episodes of hypoglycemia in pediatric patients younger than 2 years old. (1)

2 DOSAGE AND ADMINISTRATION

- Only for intravenous infusion. Do not administer subcutaneously or intramuscularly. (2.1)
- The recommended initial dose is 250 mg/kg to 500 mg/kg (1 mL/kg to 2 mL/kg). If clinically indicated, additional single doses of 250 mg/kg to 500 mg/kg (1 mL/kg to 2 mL/kg) may be administered. (2.2)
- Infusion rate depends on the age, weight, and clinical and metabolic conditions of the patient and concomitant therapy. (2.2)
- See full prescribing information for more information on preparation, administration instructions, and dosing considerations. (2.1, 2.2)

3 DOSAGE FORMS AND STRENGTHS

Injection:

1. 25% (2.5 g/10 mL) (250 mg/mL) of dextrose hydrous in a clear, colorless solution in a single-dose Ansyr™ Plastic Syringe. (3)

4 CONTRAINDICATIONS

- Intracranial or intraspinal hemorrhage. (4)
- Severe dehydration. (4)
- Hypersensitivity to dextrose. (4)

5 WARNINGS AND PRECAUTIONS

- Hyperglycemia or Hyperosmolar Hyperglycemic State: Monitor blood glucose levels before and after treatment. Use caution when selecting the dosage and injection rate due to the increased risk of hyperglycemia in neonates and low birth weight infants. (5.1)
- Hypersensitivity Reactions: Monitor for signs and symptoms and discontinue infusion immediately if reaction occurs. (5.2)
- Phlebitis and Thrombosis: Remove catheter as soon as possible if thrombophlebitis develops. (2.1, 5.3)
- Electrolyte Imbalance and Fluid Overload: Monitor changes in fluid balance, electrolyte concentrations, and acid-base balance during administration. (5.4)
- Hyponatremia: Monitor serum sodium and chloride concentrations, fluid status, acid-base balance, and neurologic status. (5.5)
- Neonatal Adverse Reactions from Unapproved Maternal Use at Time of Delivery: Maternal hyperglycemia at the time of delivery has been associated with adverse outcomes such as neonatal hypoglycemia.

6 ADVERSE REACTIONS

The most common adverse reactions are hyperglycemia, hypersensitivity reactions, hyponatremia, infection (both systemic and at the injection site), vein thrombosis, phlebitis, and electrolyte imbalance. (6)

To report SUSPECTED ADVERSE REACTIONS, contact Pfizer, Inc. at 1-800-438-1985 or FDA at 1-800-FDA-1088 or www.fda.gov/medwatch.

FULL PRESCRIBING INFORMATION

1 INDICATIONS AND USAGE

Dextrose Injection (25%) is indicated for the treatment of acute symptomatic episodes of hypoglycemia in pediatric patients from birth up to 2 years of age.

2 DOSAGE AND ADMINISTRATION

2.1 Important Preparation and Administration Instructions

- Parenteral drug products should be inspected visually for particulate matter or discoloration prior to administration. Do not use Dextrose Injection (25%) if the solution is cloudy or the seal has been broken.
- Obtain blood glucose level prior to administering Dextrose Injection (25%). However, in cases of emergency, administer Dextrose Injection (25%) promptly without awaiting blood glucose test results.
- Administer Dextrose Injection (25%) via slow intravenous injection into a central vein to reduce the risk of developing hyperglycemia and to minimize venous irritation [see Warnings and Precautions (5.1, 5.3)] .
- Do not administer Dextrose Injection (25%) simultaneously with blood through the same infusion set because pseudoagglutination of red blood cells may occur.
- Administer Dextrose Injection (25%) intravenously. Do not administer Dextrose Injection (25%) subcutaneously or intramuscularly.
- Discard the unused portion.

2.2 Recommended Dosage

The recommended initial dose of Dextrose Injection (25%) is 250 mg/kg to 500 mg/kg (1 mL/kg to 2 mL/kg). If clinically indicated, additional single doses of Dextrose Injection (25%) 250 mg/kg to 500 mg/kg (1 mL/kg to 2 mL/kg) may be administered.

Select the appropriate infusion rate based on the age, weight, and clinical and metabolic conditions of the patient.

3 DOSAGE FORMS AND STRENGTHS

Injection:

- 25% (2.5 g/10 mL) (250 mg/mL) of dextrose hydrous, in a clear, colorless solution in a single-dose Ansyr™ Plastic Syringe

4 CONTRAINDICATIONS

Dextrose Injection (25%) is contraindicated in patients with:

- Intracranial or intraspinal hemorrhage because Dextrose Injection (25%) can worsen cerebral edema by causing a fluid shift across the blood-brain barrier.
- Severe dehydration because of the potential to worsen the patient’s hyperosmolar state.
- Known hypersensitivity to dextrose [see Warnings and Precautions (5.2)].

5 WARNINGS AND PRECAUTIONS

5.1 Hyperglycemia and Hyperosmolar Hyperglycemic State

Significant hyperglycemia and hyperosmolar hyperglycemic state may result from too rapid administration of Dextrose Injection (25%). Symptoms of hyperosmolar hyperglycemic state include mental confusion and loss of consciousness. To minimize these risks, slowly inject Dextrose Injection (25%) and monitor blood glucose levels before and after treatment with Dextrose Injection (25%).

Due to the increased risk of hyperglycemia in neonates and low birth weight infants, use caution when selecting the dosage and injection rate of Dextrose Injection (25%).

5.2 Hypersensitivity Reactions

Hypersensitivity reactions, including anaphylaxis, have been reported with Dextrose Injection (25%) administration [see Adverse Reactions (6)] . Stop administration of Dextrose Injection (25%) immediately if signs or symptoms of a hypersensitivity reaction develop. Initiate appropriate treatment as clinically indicated.

5.3 Phlebitis and Thrombosis

Dextrose Injection (25%) is hypertonic (has an osmolarity greater than 900 mOsm/L) and may cause phlebitis and thrombosis at the site of injection. If thrombophlebitis occurs, remove the catheter as soon as possible.

Administer Dextrose Injection (25%) via slow intravenous injection into a central vein to reduce the risk of phlebitis and thrombosis. Ensure that the needle is well within the lumen of the vein and that extravasation does not occur. If thrombosis occurs, stop administration of Dextrose Injection (25%) and initiate corrective measures. If central venous access cannot be obtained in these pediatric patients, consider using an alternative commercially available dextrose product with a lower concentration.

Do not administer Dextrose Injection (25%) subcutaneously or intramuscularly.

5.4 Electrolyte Imbalance and Fluid Overload

Electrolyte deficits, particularly serum potassium and phosphate, may occur during prolonged use of Dextrose Injection (25%).

Depending on the administered volume and the infusion rate, administration of Dextrose Injection (25%) can cause fluid overload, including pulmonary edema.

Avoid Dextrose Injection (25%) in patients at risk for fluid and/or solute overload. If use cannot be avoided in these patients, monitor fluid balance, electrolyte concentrations, and acid base balance, especially during prolonged use. Additional monitoring is recommended for patients with water and electrolyte disturbances that could be aggravated by increased glucose, insulin administration, and/or free water load.

5.5 Hyponatremia

Dextrose Injection (25%) may cause hyponatremia. Hyponatremia can lead to acute hyponatremic encephalopathy characterized by headache, nausea, seizures, lethargy, and vomiting. The risk of hospital-acquired hyponatremia is increased in younger pediatric patients, and patients treated with diuretics, and patients with cardiac or pulmonary failure or with the syndrome of inappropriate antidiuretic hormone (SIADH) (e.g., postoperative patients, patients concomitantly treated with arginine vasopressin analogs or certain antiepileptic, psychotropic, and cytotoxic drugs) [see Drug Interactions (7.1)and Use in Specific Populations (8.4)] .

Avoid Dextrose Injection (25%) in patients with or at risk for hyponatremia. If use cannot be avoided, closely monitor serum sodium concentrations, chloride concentrations, fluid status, acid-base balance, and neurologic status [see Warnings and Precautions (5.4)] .

5.6 Neonatal Adverse Reactions from Unapproved Maternal Use at Time of Delivery

Dextrose Injection (25%) is not approved for use in adolescents or adults. Maternal hyperglycemia secondary to the use of concentrated dextrose solutions at the time of delivery has been associated with adverse outcomes such as neonatal hypoglycemia.

6 ADVERSE REACTIONS

The following clinically significant adverse reactions are also described elsewhere in the labeling:

- Hyperglycemia and Hyperosmolar Hyperglycemic State [see Warnings and Precautions (5.1)] .
- Hypersensitivity Reactions [see Warnings and Precautions (5.2)] .
- Phlebitis and Thrombosis [see Warnings and Precautions (5.3)]
- Electrolyte Imbalance and Fluid Overload [see Warnings and Precautions (5.4)]
- Hyponatremia [see Warnings and Precautions (5.5)]

The following adverse reactions associated with the use of Dextrose Injection were identified in clinical trials or postmarketing reports. Because some of these reactions were reported voluntarily from a population of uncertain size, it is not always possible to reliably estimate their frequency or establish a causal relationship to drug exposure.

- Administration site conditions:blister, extravasation, phlebitis, erythema, pain, vein damage, thrombosis
- Immune system disorders:anaphylaxis, angioedema, bronchospasm, chills, hypotension, pruritis, pyrexia, rash
- Cardiovascular disorders:cyanosis, volume overload

7 DRUG INTERACTIONS

7.1 Drugs with Effects on Glycemic Control and Electrolyte Balance

Dextrose Injection (25%) can affect glycemic control, vasopressin, and fluid and/or electrolyte balance [see Warnings and Precautions (5.1, 5.4, 5.5)] . Monitor patients’ blood glucose concentrations, fluid balance, serum electrolyte concentrations, and acid-base balance.

Concomitant administration of Dextrose Injection (25%) with drugs associated with hyponatremia may increase the risk of developing hyponatremia. Drugs associated with hyponatremia include diuretics and those that cause SIADH (e.g., selective serotonin reuptake inhibitors (SSRIs), serotonin and norepinephrine reuptake inhibitors (SNRIs), arginine vasopressin analogs, certain antiepileptic, psychotropic, and cytotoxic drugs). Avoid use of Dextrose Injection (25%) in patients receiving drugs associated with hyponatremia. If use cannot be avoided, closely monitor serum sodium concentrations during concomitant use [see Warnings and Precautions (5.5)] .

8 USE IN SPECIFIC POPULATIONS

8.4 Pediatric Use

Dextrose Injection (25%) is indicated for the treatment of acute symptomatic episodes of hypoglycemia in pediatric patients from birth up to 2 years of age.

Dextrose Injection (25%) can increase the risk of developing hypo- or hyperglycemia in neonates, especially preterm neonates with low birth weight. Excessive or rapid administration of Dextrose Injection (25%) may also result in increased serum osmolality and increase the risk of intracerebral hemorrhage in very low birth weight neonates [see Warnings and Precautions (5.1)] .

Monitor plasma electrolyte concentrations closely in pediatric patients who may have impaired ability to regulate fluids and electrolytes. Pediatric patients treated with Dextrose Injection (25%) are at increased risk of developing hyponatremia and hyponatremic encephalopathy [see Warnings and Precautions (5.4, 5.5)] .

Dextrose Injection (25%) is not indicated in pediatric patients 2 years of age and older.

10 OVERDOSAGE

A medication error resulting in a high infusion rate of Dextrose Injection (25%) can cause hyperglycemia, hyperosmolality, and adverse effects on fluid and electrolyte balance [see Warnings and Precautions (5.1, 5.4)] .

Severe hyperglycemia and severe dilutional hyponatremia, and their complications, can be fatal. In the event of overdosage (overhydration or solute overload) during Dextrose Injection (25%) treatment, discontinue the infusion. Institute corrective measures such as administration of exogenous insulin, and treat adverse effects on the CNS, respiratory, and cardiovascular systems [see Warnings and Precautions (5.1, 5.4)] .

11 DESCRIPTION

Dextrose, USP is chemically designated D-glucose monohydrate, (C6H12O6• H2O), a hexose sugar freely soluble in water, with the following structural formula:

Water for Injection, USP is chemically designated H2O. The molecular weight of dextrose (D-glucose) monohydrate is 198.17.

Dextrose Injection, USP (25%) is a sterile, nonpyrogenic, hypertonic solution of dextrose in water for intravenous injection.

Each milliliter (mL) of fluid contains 0.25 grams of dextrose, hydrous, which delivers 3.4 kcal/gram (0.85 kcal/mL). The solution has an osmolarity of 1.39 mOsmol/mL (calculation) and the pH range is 3.2 to 6.5. May contain hydrochloric acid and sodium hydroxide for pH adjustment.

The solution contains no bacteriostatic, antimicrobial agent or added buffer (except for pH adjustment) and is supplied in a single-dose Ansyr™ Plastic Syringe.

Dextrose is derived from corn.

12 CLINICAL PHARMACOLOGY

12.1 Mechanism of Action

Dextrose restores blood glucose levels and provides a source of carbohydrate calories.

12.2 Pharmacodynamics

The exposure-response relationship and time course of pharmacodynamic response for the safety and effectiveness of dextrose have not been fully characterized.

12.3 Pharmacokinetics

Dextrose is oxidized to carbon dioxide and water.

13 NONCLINICAL TOXICOLOGY

13.1 Carcinogenesis, Mutagenesis, Impairment of Fertility

Studies with dextrose to evaluate the drug’s carcinogenic potential, mutagenic potential or effects on fertility have not been performed.

16 HOW SUPPLIED/STORAGE AND HANDLING

Dextrose Injection, USP (25%) is supplied as a clear, colorless solution in single-dose syringe as follows:

NDC: 70518-4452-00

NDC: 70518-4452-01

PACKAGING: 1 in 1 CARTON

PACKAGING: 10 mL in 1 SYRINGE, PLASTIC TYPE 2

Store at 20°C to 25°C (68°F to 77°F) [See USP Controlled Room Temperature.]

Repackaged and Distributed By:

Remedy Repack, Inc.

625 Kolter Dr. Suite #4 Indiana, PA 1-724-465-8762

PACKAGE LABEL

DRUG: Dextrose

GENERIC: Dextrose monohydrate

DOSAGE: INJECTION, SOLUTION

ADMINSTRATION: INTRAVENOUS

NDC: 70518-4452-0

NDC: 70518-4452-1

PACKAGING: 10 mL in 1 SYRINGE, PLASTIC

OUTER PACKAGING: 1 in 1 CARTON

ACTIVE INGREDIENT(S):

- DEXTROSE MONOHYDRATE 250mg in 1mL

INACTIVE INGREDIENT(S):

- WATER
- SODIUM HYDROXIDE
- HYDROCHLORIC ACID